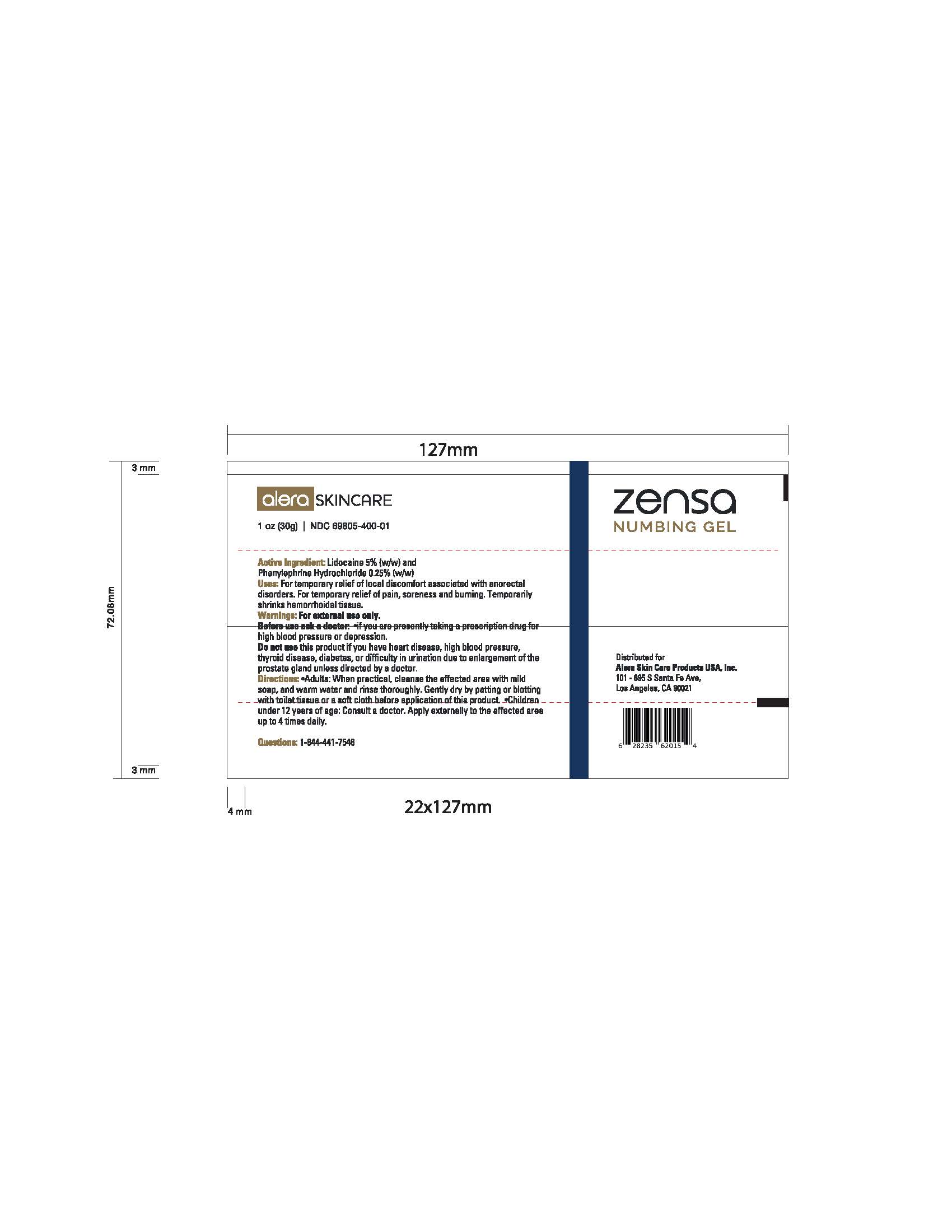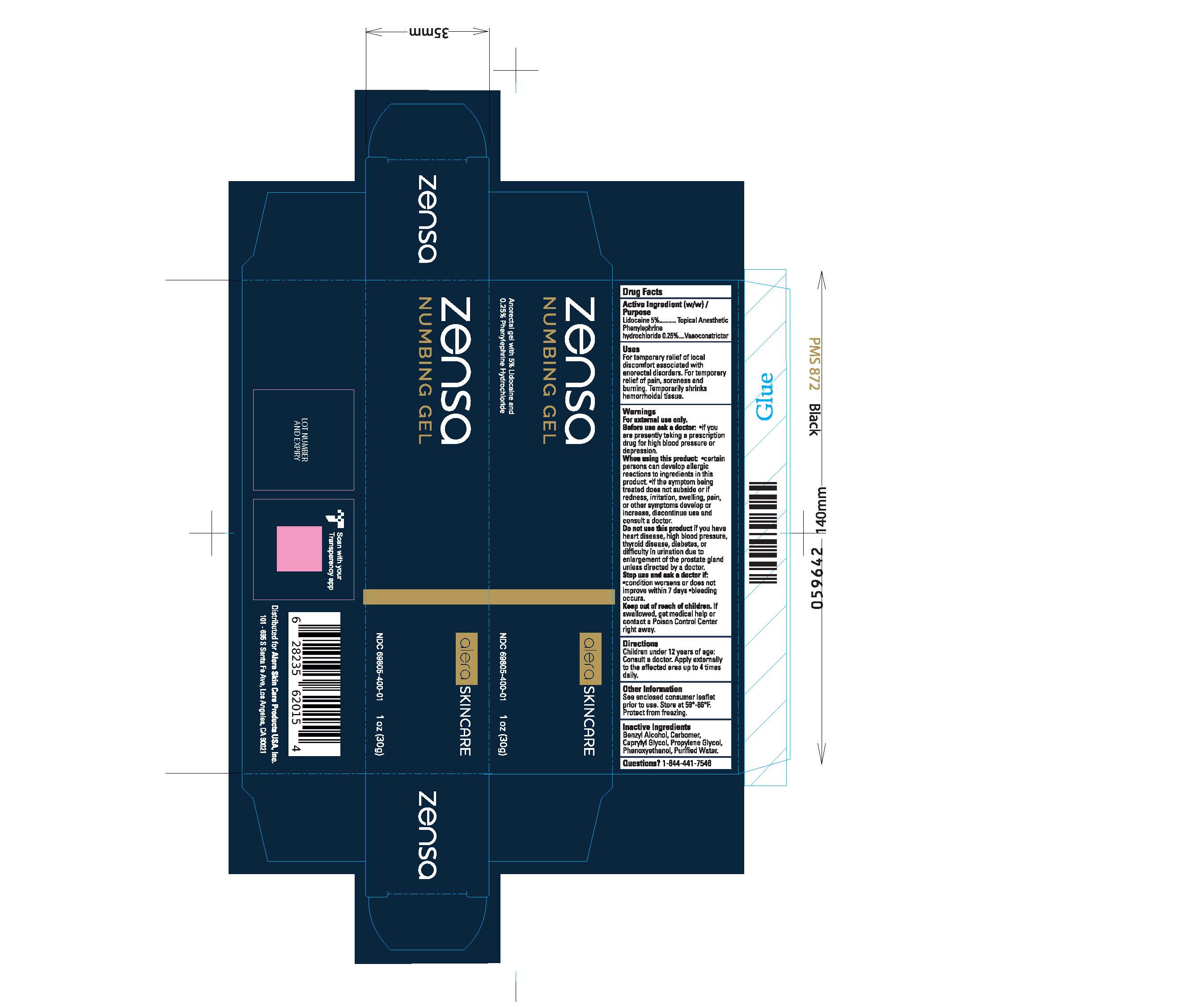 DRUG LABEL: Zensa Numbing Gel
NDC: 69805-400 | Form: GEL
Manufacturer: Alera Skin Care Products Inc.
Category: otc | Type: HUMAN OTC DRUG LABEL
Date: 20230927

ACTIVE INGREDIENTS: PHENYLEPHRINE HYDROCHLORIDE 0.25 g/100 g; LIDOCAINE 5 g/100 g
INACTIVE INGREDIENTS: CAPRYLYL GLYCOL; PROPYLENE GLYCOL; BENZYL ALCOHOL; CARBOMER HOMOPOLYMER TYPE B (ALLYL PENTAERYTHRITOL CROSSLINKED); PHENOXYETHANOL; WATER

Active Ingredient

Lidocaine 5% and Phenylephrine hydrochloride 0.25%

PURPOSE

Local Anaesthetic

Vasoconstrictor

Protective

USES

For temporary relief of local discomfort associated with anorectal disorders. For temporary
relief of pain, soreness and burning. Temporarily shrinks hemorrhoidal tissue.

WARNINGS

For external use only.

Before use ask a doctor:
•if you are presently taking a prescription drug for high blood pressure or depression.

When using this product:

•certain persons can develop allergic reactions to ingredients in this product.
•if the symptom being treated does not subside or if redness, irritation, swelling, pain, or other symptoms develop or increase, discontinue use and consult a doctor.

Do not use this product if you have
heart disease, high blood pressure, thyroid disease, diabetes, or difficulty in urination due to enlargement of the prostate gland
unless directed by a doctor.

Stop use and ask a doctor if:

•condition worsens or does not improve within 7 days

•bleeding occurs.

KEEP OUT OF REACH OF CHILDREN

If swallowed, get medical help or contact a Poison Control Center right away.

DIRECTIONS

Children under 12 years of age: Consult a doctor.

Apply externally to the affected area up to 4 times daily.

STORAGE AND HANDLING

Other Information

See enclosed consumer leaflet prior to use. Store at 59°-86°F.
Protect from freezing.

INACTIVE INGREDIENT

Benzyl Alcohol, Carbomer, Caprylyl Glycol, Propylene Glycol, Phenoxyethanol, Purified Water.

QUESTIONS

Questions? 1-844-441-7546